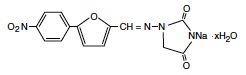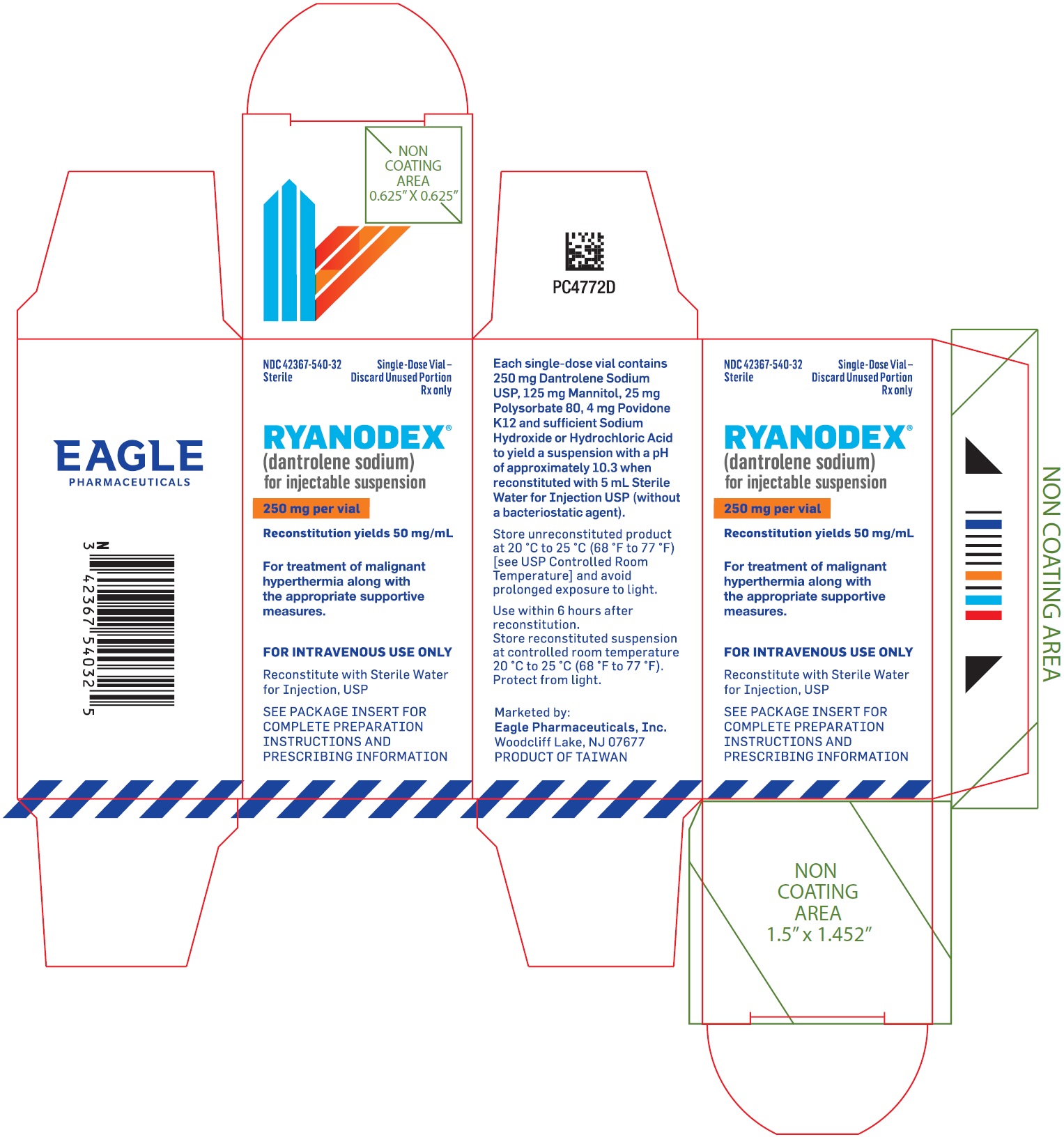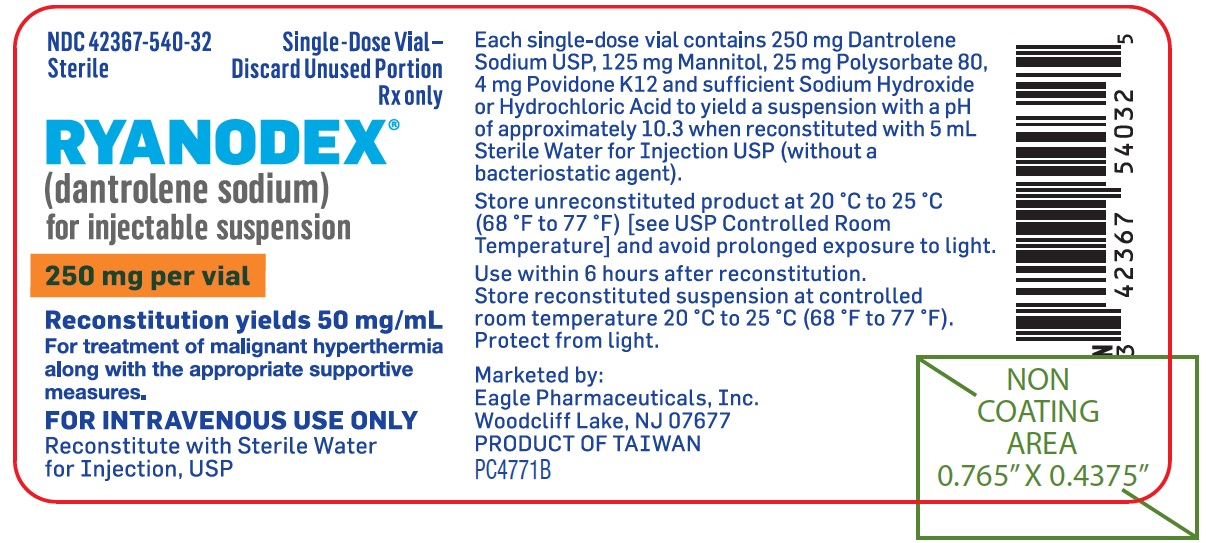 DRUG LABEL: RYANODEX 
NDC: 42367-540 | Form: INJECTION, SUSPENSION
Manufacturer: Eagle Pharmaceuticals, Inc.
Category: prescription | Type: HUMAN PRESCRIPTION DRUG LABEL
Date: 20241030

ACTIVE INGREDIENTS: DANTROLENE SODIUM 250 mg/5 mL
INACTIVE INGREDIENTS: MANNITOL; POVIDONE K12; POLYSORBATE 80; HYDROCHLORIC ACID; SODIUM HYDROXIDE; NITROGEN; WATER

HIGHLIGHTS OF PRESCRIBING INFORMATION

These highlights do not include all the information needed to use RYANODEX safely and effectively. See full prescribing information for RYANODEX.
RYANODEX® (dantrolene sodium) for injectable suspension, for intravenous use.
Initial U.S. Approval: 1974

1 INDICATIONS AND USAGE

RYANODEX is a skeletal muscle relaxant drug indicated for:

- Treatment of malignant hyperthermia in conjunction with appropriate supportive measures. (1)
- Prevention of malignant hyperthermia in patients at high risk. (1)

2 DOSAGE AND ADMINISTRATION

- Treatment of Malignant Hyperthermia (MH) (2.1)
  - Administer by intravenous push at a minimum of 1 mg/kg. If signs continue, administer additional intravenous boluses up to maximum cumulative dosage of 10 mg/kg.
  - Institute supportive measures (e.g., discontinue MH-triggering agents, manage metabolic acidosis, cooling if necessary, administer diuretics)
- Prevention of MH in Patients at High Risk (2.2)
  - Administer 2.5 mg/kg intravenously over a period of at least 1 minute, starting approximately 75 minutes prior to surgery.
  - Avoid agents that trigger MH.
  - Administer additional individualized doses during anesthesia and surgery if surgery is prolonged.
- Pediatric Patients: recommended weight-based dose is the same as for adults (2.3)
- Reconstitution: With 5 mL of sterile water for injection (without a bacteriostatic agent) prior to administration (2.4)

3 DOSAGE FORMS AND STRENGTHS

For injectable suspension: 250 mg of lyophilized powder in a single-dose vial for reconstitution (3)

4 CONTRAINDICATIONS

None (4)

5 WARNINGS AND PRECAUTIONS

- Skeletal Muscle Weakness: Ambulate patients with assistance until they have normal strength and balance (5.1)
- Dyspnea, Respiratory Muscle Weakness, and Decreased Inspiratory Capacity: Monitor patients for the adequacy of ventilation (5.1)
- Dysphagia: Assess patients for difficulty swallowing and choking (5.1)
- Somnolence and Dizziness: Can occur following RYANODEX administration; may persist up to 48 hours post-dose. Ambulate patients with assistance until they have normal strength and balance (5.2)
- Tissue Necrosis with Extravasation: Due to high pH of reconstituted RYANODEX for injectable suspension, care must be taken to prevent extravasation into surrounding tissues (5.3)

6 ADVERSE REACTIONS

- Administration to conscious subjects is associated with loss of grip strength and weakness in the legs, drowsiness and dizziness.
- Other common adverse reactions are: nausea, thrombophlebitis, tissue necrosis secondary to extravasation, urticaria and erythema, and injection site reactions (pain, erythema, swelling) (6.1)

To report SUSPECTED ADVERSE REACTIONS, contact Eagle at
1-855-318-2170 or FDA at 1-800-FDA-1088 or www.fda.gov/medwatch.

7 DRUG INTERACTIONS

- Calcium Channel Blockers: Concomitant use can cause cardiovascular collapse in association with marked hyperkalemia (7.1)
- Muscle Relaxants: Concomitant use with muscle relaxants may potentiate their effects (7.2)
- Sedatives: Concomitant use with sedative agents may potentiate their effects (7.3)

8 USE IN SPECIFIC POPULATIONS

- Pregnancy: Based on animal data, may cause fetal harm); however, RYANODEX administration for malignant hyperthermia may be lifesaving for the pregnant woman and fetus. Treatment should not be withheld due to pregnancy (8.1)
- Lactation: Breastfeeding is not recommended during treatment with RYANODEX and for 3 days after the final dose. (8.2)

FULL PRESCRIBING INFORMATION

1 INDICATIONS AND USAGE

RYANODEX® is indicated for the:

- Treatment of malignant hyperthermia in conjunction with appropriate supportive measures [see Dosage and Administration (2.1)]
- Prevention of malignant hyperthermia in patients at high risk.

2 DOSAGE AND ADMINISTRATION

2.1 Dosage for Treatment of Malignant Hyperthermia

In addition to RYANODEX treatment, institute the following supportive measures:

- Discontinue use of malignant hyperthermia (MH)-triggering anesthetic agents (i.e., volatile anesthetic gases and succinylcholine).
- Manage the metabolic acidosis
- Institute cooling when necessary
- Administer diuretics to prevent late kidney injury due to myoglobinuria (the amount of mannitol in RYANODEX is insufficient to maintain diuresis) [see Description (11)]

Administer RYANODEX by intravenous push at a minimum dose of 1 mg/kg. If the physiologic and metabolic abnormalities of MH continue, administer additional intravenous boluses up to the maximum cumulative dosage of 10 mg/kg.

If the physiologic and metabolic abnormalities reappear, repeat RYANODEX dosing by intravenous push starting with 1 mg/kg.

2.2 Dosage for Prevention of Malignant Hyperthermia

The recommended prophylactic dose of RYANODEX is 2.5 mg/kg administered intravenously over a period of at least 1 minute, starting approximately 75 minutes prior to surgery. Avoid agents that trigger MH.

If surgery is prolonged, administer additional individualized RYANODEX doses during anesthesia and surgery [see Clinical Pharmacology (12.3)].

2.3 Dosage for Pediatric Patients

The recommended weight-based dose of RYANODEX for pediatric patients in the treatment and prevention of MH is the same as for adults for these indications [see Dosage and Administration (2.1, 2.2)].

2.4 Reconstitution and Administration Instructions

The supplied lyophilized powder must be reconstituted prior to administration:

(a) Reconstitute each vial of RYANODEX lyophilized powder by adding 5 mL of sterile water for injection (without a bacteriostatic agent). Do not reconstitute with any other solution (e.g., 5% dextrose injection, 0.9% sodium chloride injection).
(b) Shake the vial to ensure an orange-colored uniform suspension. Visually inspect the vial for particulate matter and discoloration prior to administration.
(c) Must use the contents of the vial within 6 hours after reconstitution. Store reconstituted suspensions at controlled room temperature (68°F to 77°F or 20°C to 25°C).

Do not dilute or transfer the reconstituted RYANODEX suspension to another container to infuse the product.

Administer the reconstituted RYANODEX suspension either:

- Into the intravenous catheter while an intravenous infusion of 0.9% sodium chloride injection, or 5% dextrose injection is freely running; or
- Into the indwelling catheter - after assuring its patency - without a freely running infusion. Flush the line to assure that there is no residual RYANODEX remaining in the catheter [see Warnings and Precautions (5.3)].

3 DOSAGE FORMS AND STRENGTHS

For injectable suspension: RYANODEX is a sterile, lyophilized powder containing 250 mg of dantrolene sodium for reconstitution, in single-dose vials

4 CONTRAINDICATIONS

None

5 WARNINGS AND PRECAUTIONS

5.1 Muscle Weakness

RYANODEX is associated with skeletal muscle weakness. The administration of RYANODEX in human volunteers has been associated with loss of grip strength and weakness in the legs. Patients should not be permitted to ambulate without assistance until they have normal strength and balance.

RYANODEX has been associated with dyspnea, respiratory muscle weakness, and decreased inspiratory capacity. Monitor patients for the adequacy of ventilation.

RYANODEX has been associated with dysphagia. Assess patients for difficulty swallowing and choking.

5.2 Somnolence and Dizziness

Somnolence and dizziness can occur following administration of RYANODEX and may persist up to 48 hours post-dose. Patients should not be permitted to ambulate without assistance until they have normal strength and balance. Patients must not operate an automobile or engage in other hazardous activities for 48 hours post-dose.

The concomitant use of sedative agents with RYANODEX may increase the risk of somnolence and dizziness.

5.3 Potential for Tissue Necrosis with Extravasation

Care must be taken to prevent extravasation of RYANODEX into the surrounding tissues due to the high pH of the reconstituted RYANODEX suspension and potential for tissue necrosis.

6 ADVERSE REACTIONS

6.1 Clinical Trials Experience

Because clinical trials are conducted under widely varying conditions, adverse reaction rates observed in the clinical trials of a drug cannot be directly compared to rates in the clinical trials of another drug and may not reflect the rates observed in practice.

In a study designed to evaluate the safety and tolerability of RYANODEX, healthy volunteers were randomly assigned to receive treatment with RYANODEX or an active comparator at doses ranging from 1 mg/kg to 2.5 mg/kg.

- The RYANODEX dose was infused over the course of 1 minute for each of the doses evaluated.
- The active comparator was an injectable formulation of dantrolene sodium that differed from RYANODEX in that it contained dantrolene sodium and mannitol at concentrations of 0.33 mg/mL and 50 mg/mL, respectively, when reconstituted according to the product's prescribing information. The active comparator was infused at a rate that administered 20 mg of dantrolene per minute for each of the doses evaluated.

Table 1 displays the most common adverse events in this study. These data are not an adequate basis for comparison of the types or frequencies of adverse event types between RYANODEX and the dantrolene sodium comparator.

Adverse events increased in frequency with increasing doses in the trial, but did not differ in frequency between the two treatment groups. RYANODEX-treated subjects were more likely to report immediate adverse events of flushing, dystonia, and dysphagia than those receiving the active comparator.

In all dose groups, hand grip strength declined after dosing. In general, the decline in hand grip strength was more pronounced and occurred more rapidly in the RYANODEX-treated subjects in the 1.0, 1.75, 2.0 and 2.25 mg/kg treatment groups. In the 2.5 mg/kg treatment group, the decline in hand grip strength both in amount and duration was similar between the two treatment groups.

Table 1: Adverse Events in Healthy Volunteers
 | Number of subjects (%)
 | RYANODEX [N=30] n (%) | Dantrolene Sodium Comparator [N=31] n (%)
Flushing | 8 (27) | 1 (3)
Somnolence | 5 (17) | 4 (13)
Dysphonia | 4 (13) | 1 (3)
Dysphagia | 3 (10) | 4 (13)
Nausea | 3 (10) | 3 (10)
Feeling abnormal | 3 (10) | 3 (10)
Headache | 1 (3) | 4 (13)
Vomiting | 1 (3) | 2 (6)
Vision blurred | 1 (3) | 1 (3)
Pain in extremity | 1 (3) | 1 (3)
Muscular weakness/Asthenia | 1 (3) | 1 (3)
Atrioventricular block | 1 (3) | 0
Tachycardia | 1 (3) | 0
Infusion site pain | 1 (3) | 0
Dizziness | 1 (3) | 0

6.2 Postmarketing Experience

The following adverse reactions have been identified during postapproval use of another formulation of dantrolene sodium for injection. Because these reactions are reported voluntarily from a population of uncertain size, it is not always possible to reliably estimate their frequency or establish a causal relationship to drug exposure.

Pulmonary Edema
There have been reports of pulmonary edema developing during the treatment of malignant hyperthermia crises with another dantrolene sodium dosage form. The contributory effect of the diluent volume and mannitol in these cases is not known.

Thrombophlebitis and Tissue Necrosis
There have been reports of thrombophlebitis following administration of intravenous dantrolene. Tissue necrosis secondary to extravasation has been reported [see Warnings and Precautions (5.3)].

Hypersensitivity/Anaphylactic Reactions
There have been reports of urticaria and erythema possibly associated with the administration of dantrolene sodium for injection. Anaphylaxis has been reported.

Injection Site Reactions
Injection site reactions including pain, erythema, and swelling, commonly due to extravasation, have been reported.

Hepatotoxicity
Cases of hepatotoxicity following the use of intravenous dantrolene products have been reported. Elevated liver enzymes have occurred hours to days following use of intravenous dantrolene, though many of these cases were observed in patients with comorbidities (e.g., critical illness).

7 DRUG INTERACTIONS

7.1 Calcium Channel Blockers

Cardiovascular collapse in association with marked hyperkalemia has been reported in patients receiving dantrolene in combination with calcium channel blockers. The concomitant use of RYANODEX and calcium channel blockers is not recommended during the treatment of malignant hyperthermia.

7.2 Muscle Relaxants

The concomitant administration of RYANODEX with muscle relaxants may potentiate the neuromuscular block.

7.3 Antipsychotics and Antianxiety Agents

The concomitant administration of RYANODEX with antipsychotic and antianxiety agents may potentiate their effects on the central nervous system [see Warnings and Precautions (5.2)].

8 USE IN SPECIFIC POPULATIONS

8.1 Pregnancy

Risk Summary
Available data from published case reports with RYANODEX use in pregnant women are insufficient to evaluate for a drug-associated risk of major birth defects, miscarriage, or adverse maternal or fetal outcomes. Dantrolene readily crosses the placenta; however, no serious adverse events have been reported in the neonate following maternal administration of dantrolene prior to delivery. There are risks to the pregnant woman and fetus associated with untreated malignant hyperthermia (see Clinical Considerations). In animal reproduction studies, dantrolene sodium administered to rats and rabbits produced embryolethality (rabbits) and decreased pup survival (rats) at doses seven times the human oral dose (see Data).

The estimated background risk of major birth defects and miscarriage for the indicated population is unknown. All pregnancies have a background risk of birth defect, loss, or other adverse outcomes. In the U.S. general population, the estimated background risk of major birth defects and miscarriage in clinically recognized pregnancies is 2 to 4% and 15 to 20%, respectively.

Clinical Considerations
Disease-associated maternal and embryo/fetal risk
Malignant hyperthermia is a medical emergency which can be fatal for the pregnant woman and fetus if left untreated. Life-sustaining therapy should not be withheld due to pregnancy.

Labor or Delivery
In one uncontrolled study, 100 mg per day of prophylactic oral dantrolene sodium was administered to term pregnant patients awaiting labor and delivery. Dantrolene readily crossed the placenta, with maternal and fetal whole blood levels approximately equal at delivery; neonatal levels then fell approximately 50% per day for 2 days before declining sharply. No neonatal respiratory and neuromuscular side effects were observed in this study.

Data
Animal Data
Animal reproduction studies have been conducted with dantrolene sodium. In these studies, dantrolene sodium administered to rats and rabbits produced embryolethality (rabbits) and decreased pup survival (rats) at doses seven times the human oral dose.

8.2 Lactation

Risk Summary
Dantrolene is reported to be present in human milk following intravenous administration over 3 days. There are no data on the effects on the breastfed infant or the effects on milk production. Because of the potential for serious adverse reactions in the breastfed infant, including respiratory depression and muscle weakness, advise patients that breastfeeding is not recommended during treatment with RYANODEX, and for 3 days after the last dose.

Clinical Considerations
A lactating woman should interrupt breastfeeding and pump and discard breast milk during treatment and for 3 days after RYANODEX administration.

8.4 Pediatric Use

The safety and efficacy of RYANODEX in the treatment and prevention of malignant hyperthermia in pediatric patients is based on clinical experience with other intravenous dantrolene sodium products, which suggests adult weight-based doses are appropriate for pediatric patients.

8.5 Geriatric Use

Clinical studies of RYANODEX did not include sufficient numbers of subjects aged 65 and over to determine whether they respond differently from younger subjects. Other reported clinical experience has not identified differences in responses between the elderly and younger patients. In general, dose selection for an elderly patient should be cautious reflecting the greater frequency of decreased hepatic, renal, or cardiac function, and of concomitant disease or other drug therapy.

10 OVERDOSAGE

10.1 Overdosage Symptoms

Overdosage symptoms include, but are not limited to, muscular weakness and alterations in the state of consciousness (e.g., lethargy, coma), vomiting, diarrhea, and crystalluria.

10.2 Management of Overdosage

Employ general supportive measures for acute overdosage of RYANODEX.

Administer intravenous fluids in fairly large quantities to avert the possibility of crystalluria. Maintain an adequate airway and keep artificial resuscitation equipment available. Institute electrocardiographic monitoring and carefully observe the patient. The value of dialysis in RYANODEX overdosage is not known.

11 DESCRIPTION

RYANODEX® (dantrolene sodium) for injectable suspension is a sterile lyophilized powder. RYANODEX is supplied in 20 mL vials containing 250 mg dantrolene sodium and the following inactive ingredients: 125 mg mannitol, 25 mg polysorbate 80, 4 mg povidone K12 and sufficient sodium hydroxide or hydrochloric acid for pH adjustment. When reconstituted with 5 mL sterile water for injection USP (without a bacteriostatic agent), this yields a suspension with a pH of approximately 10.3.

RYANODEX is a skeletal muscle relaxant. Chemically, RYANODEX is a hydrate of 1-[[[5-(4-nitrophenyl)-2-furanyl]methylene]amino]-2,4-imidazolidinedione sodium salt. The structural formula for the hydrated salt is:

The hydrated salt contains approximately 15% water (3-1/2 moles) and has a molecular weight of 399. The anhydrous salt (dantrolene) has a molecular weight of 336.

12 CLINICAL PHARMACOLOGY

12.1 Mechanism of Action

In isolated nerve-muscle preparation, dantrolene has been shown to produce relaxation by affecting the contractile response of the muscle at a site beyond the myoneural junction. In skeletal muscle, dantrolene dissociates the excitation-contraction coupling, probably by interfering with the release of Ca^++ from the sarcoplasmic reticulum.

In the anesthetic-induced malignant hyperthermia syndrome, evidence points to an intrinsic abnormality of skeletal muscle tissue. In affected humans, it has been postulated that “triggering agents” (e.g., general anesthetics and depolarizing neuromuscular blocking agents) produce a change within the cell which results in an elevated myoplasmic calcium. This elevated myoplasmic calcium activates acute cellular catabolic processes that cascade to the malignant hyperthermia crisis.

The addition of dantrolene to the “triggered” malignant hyperthermic muscle cell may reestablish a normal level of ionized calcium in the myoplasm. Inhibition of calcium release from the sarcoplasmic reticulum by dantrolene reestablishes the myoplasmic calcium equilibrium, increasing the percentage of bound calcium. In this way, physiologic, metabolic, and biochemical changes associated with the malignant hyperthermia crisis may be reversed or attenuated.

12.2 Pharmacodynamics

The administration of intravenous dantrolene to human volunteers was associated with loss of grip strength and weakness in the legs, as well as subjective CNS complaints [see Warnings and Precautions (5.1)].

12.3 Pharmacokinetics

The pharmacokinetics of RYANODEX was investigated in healthy volunteers following single-dose administration as an intravenous push over 60 seconds (dose range of 1 to 2.5 mg/kg), via a peripheral catheter. There was a dose-proportional increase in plasma exposure of dantrolene and its metabolite, 5-hydroxydantrolene. Table 2 presents pharmacokinetic parameters of dantrolene after administration of a single RYANODEX dose of 2.5 mg/kg. Time to peak dantrolene concentration was observed at the first time point collected (i.e., median Tmax is 1 minute post-dose). The mean half-life (t1/2) for dantrolene was independent of the RYANODEX dose administered and ranged from 8.5 hours to 11.4 hours over the 1 to 2.5 mg/kg dose range.

Table 2: Pharmacokinetic Parameters for Dantrolene in Healthy Volunteers (Mean ± Standard Deviation)
RYANODEX dose^1 | Cmax (μg/mL) | AUC0-inf (μg*h/mL) | Half-life (hrs) | Clearance (L/hr) | Volume of distribution (L)
2.5 mg/kg | 9.0 ± 4.6 | 77.7 ± 23.2 | 10.8 ± 2.2 | 2.5 ± 1.0 | 36.4 ± 11.7
^1 n=15; single-dose

When prophylactic intravenous dantrolene infusion was administered, whole blood dantrolene concentrations remained at a near steady state level for 3 or more hours after the infusion was completed.

Distribution
Based on assays of whole blood and plasma, slightly greater amounts of dantrolene are associated with red blood cells than with the plasma fraction of blood. Significant amounts of dantrolene are bound to plasma proteins, mostly albumin, and this binding is readily reversible. Binding to plasma protein is not significantly altered by diazepam, diphenylhydantoin, or phenylbutazone. Binding to plasma proteins is reduced by warfarin and clofibrate and increased by tolbutamide.

Information concerning the passage of dantrolene across the blood-brain barrier is not available.

Metabolism
Dantrolene is found in measurable amounts in blood and urine. Its major metabolites in body fluids are 5-hydroxy dantrolene and an acetylamino metabolite of dantrolene. Another metabolite with an unknown structure appears related to the latter. Dantrolene may also undergo hydrolysis and subsequent oxidation forming nitrophenylfuroic acid. Following RYANODEX 2.5 mg/kg dose administration in healthy volunteers, mean peak plasma concentration for the primary metabolite, 5-hydroxydantrolene, was 640 ng/mL, and was achieved by approximately 24 hours post-dose, with an average metabolite-to-parent exposure ratio of 0.27 (AUC0-inf = 21.2 μg*h/mL). Median t1/2 for 5-hydroxydantrolene was 10 hours, the clearance was estimated to be 8.9 L/hr and the terminal phase volume of distribution was 144 L.

Dantrolene is metabolized by the liver, and it is possible that its metabolism may be enhanced by drugs known to induce hepatic microsomal enzymes. However, neither phenobarbital nor diazepam appears to affect dantrolene metabolism.

13 NONCLINICAL TOXICOLOGY

13.1 Carcinogenesis, Mutagenesis, Impairment of Fertility

Carcinogenesis

Sprague-Dawley female rats fed dantrolene sodium for 18 months at dosage levels of 15, 30, and 60 mg/kg/day showed an increased incidence of benign and malignant mammary tumors compared with concurrent controls. At the highest dose level (approximately the same as the maximum recommended daily human dose on a mg/m^2 basis), there was an increase in the incidence of benign hepatic lymphatic neoplasms. In a 30-month study in Sprague-Dawley rats fed dantrolene sodium, the highest dose level (approximately the same as the maximum recommended daily human dose on a mg/m^2 basis) produced a decrease in the time of onset of mammary neoplasms. Female rats at the highest dose level showed an increased incidence of hepatic lymphangiomas and hepatic angiosarcomas.

The only drug-related effect seen in a 30-month study in Fischer-344 rats was a dose-related reduction in the time of onset of mammary and testicular tumors. A 24-month study in HaM/ICR mice revealed no evidence of carcinogenic activity.

The significance of carcinogenicity data relative to use of RYANODEX in humans is unknown.

Mutagenesis

Dantrolene sodium has produced positive results in the Ames S. Typhimurium bacterial mutagenesis assay in the presence and absence of a liver activating system.

Impairment of Fertility

Dantrolene sodium administered to male and female rats at dose levels up to 45 mg/kg/day (approximately 1.4 times the maximum recommended daily human dose on a mg/m^2 basis) showed no adverse effects on fertility or general reproductive performance.

16 HOW SUPPLIED/STORAGE AND HANDLING

RYANODEX® (NDC 42367-540-32) is available in 20 mL vials containing a sterile lyophilized mixture of 250 mg dantrolene sodium for reconstitution with 5 mL sterile water for injection USP (without a bacteriostatic agent) to yield an orange colored injectable suspension.

Store unreconstituted product at 20 °C to 25 °C (68 ºF to 77 ºF) [see USP Controlled Room Temperature], with excursions permitted to 15 ºC to 30 ºC (59 ºF to 86 ºF) and avoid prolonged exposure to light.

17 PATIENT COUNSELING INFORMATION

Inform patients, their families, or their caregivers of the following:

Muscle Weakness
Muscle weakness (i.e., decrease in grip strength and weakness of leg muscles, especially walking down stairs) is likely to occur with the use of RYANODEX. Patients should be provided assistance with standing and walking until their strength has returned to normal [see Warnings and Precautions (5.1)].

Difficulty Swallowing
Caution is indicated at meals on the day of administration because difficulty swallowing and choking have occurred with the use of dantrolene sodium products in general; dysphagia has been reported with the use of RYANODEX [see Warnings and Precautions (5.1)].

Dizziness and Somnolence
The use of RYANODEX has been associated with dizziness and somnolence. [see Warnings and Precautions (5.2)].

Driving or Operating Machinery
Symptoms such as “lightheadedness” may occur. Since some of these symptoms may persist for up to 48 hours, patients must not operate an automobile or engage in other hazardous activity during this time [see Warnings and Precautions (5.2)].

Lactation
Advise females not to breastfeed during treatment with RYANODEX and for 3 days after the final dose [see Use in Specific Populations (8.2)].

Marketed by:
Eagle Pharmaceuticals, Inc.
Woodcliff Lake, NJ 07677

PRINCIPAL DISPLAY PANEL - NDC: 42367-540-32 - Carton Label

NDC 42367-540-32
Sterile

Single Use Only -
Discard Unused Portion
Rx only

Ryanodex®
(dantrolene sodium)
for injectable suspension

250 mg per vial

Reconstitution yields 50 mg/mL

For treatment of malignant hyperthermia, along with the appropriate supportive measures.

For intravenous use only

Reconstitute with Sterile Water for Injection, USP

SEE PACKAGE INSERT FOR COMPLETE PREPARATION INSTRUCTIONS AND PRESCRIBING INFORMATION.

PRINCIPAL DISPLAY PANEL - NDC: 42367-540-32 - Vial Label

NDC 42367-540-32
Sterile

Single Use Only -
Discard Unused Portion
Rx only

Ryanodex®
(dantrolene sodium)
for injectable suspension

250 mg per vial

Reconstitution yields 50 mg/mL

For treatment of malignant hyperthermia, along with the appropriate supportive measures.

For Intravenous Use Only

Reconstitute with Sterile Water for Injection, USP